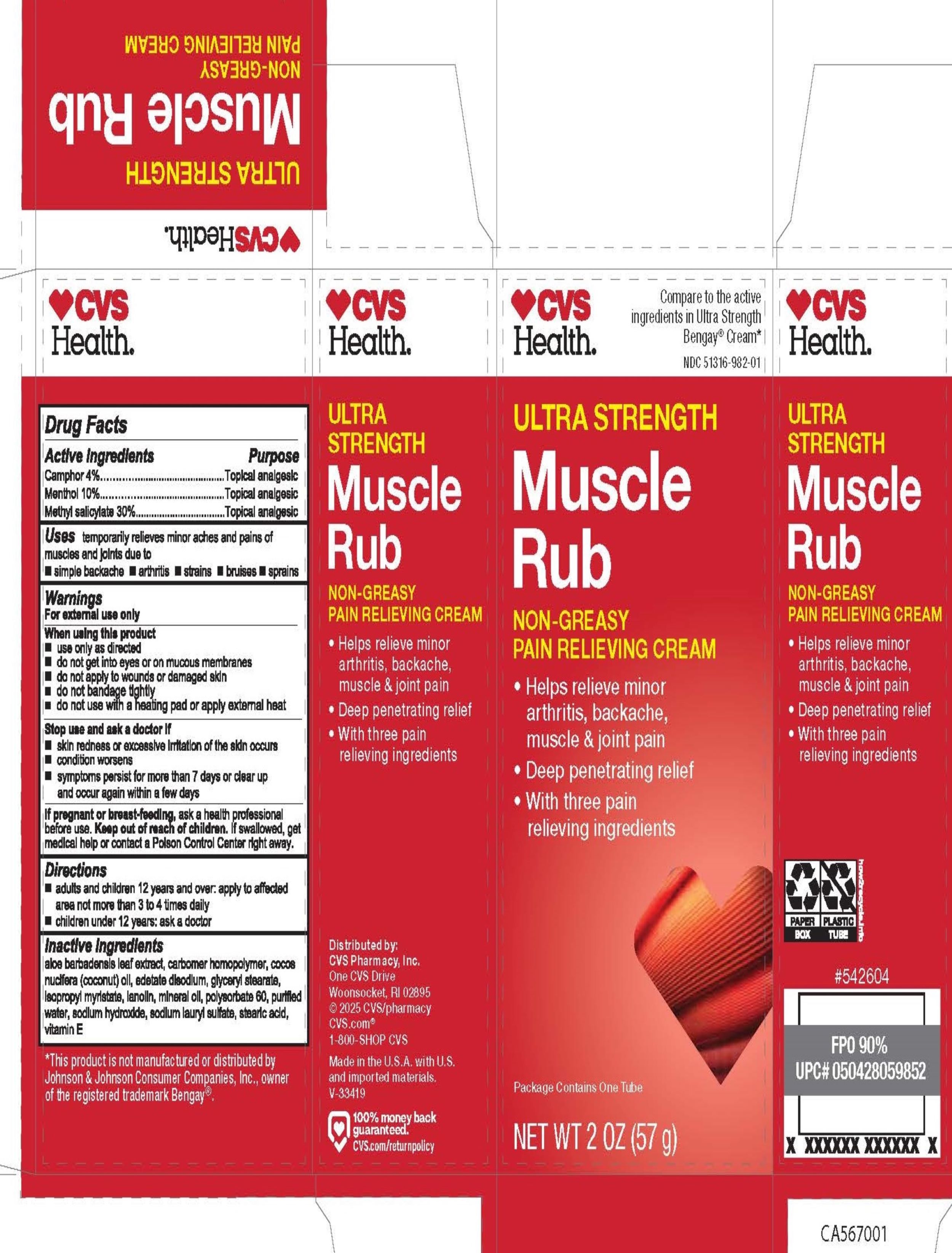 DRUG LABEL: Ultra Strength Muscle Rub - CVS Health
NDC: 51316-982 | Form: CREAM
Manufacturer: CVS Pharmacy
Category: otc | Type: HUMAN OTC DRUG LABEL
Date: 20250221

ACTIVE INGREDIENTS: CAMPHOR (SYNTHETIC) 40 mg/1 g; METHYL SALICYLATE 300 mg/1 g; MENTHOL 100 mg/1 g
INACTIVE INGREDIENTS: COCOS NUCIFERA (COCONUT) OIL; WATER; SODIUM HYDROXIDE; EDETATE DISODIUM; LANOLIN; POLYSORBATE 60; STEARIC ACID; GLYCERYL STEARATE; MINERAL OIL; ISOPROPYL MYRISTATE; ALOE BARBADENSIS LEAF; SODIUM LAURYL SULFATE; CARBOMER HOMOPOLYMER TYPE C; VITAMIN E POLYETHYLENE GLYCOL SUCCINATE

Drug Facts - Ultra Strength Muscle Rub

Active ingredient

Camphor 4%

Menthol 10%

Methyl salicylate 30%

Purpose

Camphor - Topical analgesic

Menthol - Topical analgesic

Methyl salicylate - Topical analgesic

Uses

- simple backache
- arthritis
- strains
- bruises
- sprains

Warnings

For external use only

When using this product

- use only as directed
- do not get into eyes or on mucous membranes
- do not apply to wounds or damaged skin
- do not bandage tightly
- do not use with a heating pad or apply external heat

Stop use and ask a doctor if

- skin redness or excessive irritation of the skin occurs
- condition worsens
- symptoms persist for more than 7 days or clear up and occur again within a few days

If pregnant or breast feeding,

ask a health professional before use.

Keep out of reach of children

If swallowed, get medical help or contact a Poison Control Center right away.

Directions

- adults and children 12 years and over: apply to affected area not more than 3 to 4 times daily
- children under 12 years: ask a doctor

Inactive ingredients

aloe barbadensis leaf extract, carbomer homopolymer, cocos nucifera (coconut) oil, edetate disodium, glyceryl stearate, isopropyl myristate, lanolin, mineral oil, polysorbate 60, purified water, sodium hydroxide, sodium lauryl sulfate, stearic acid, vitamin E